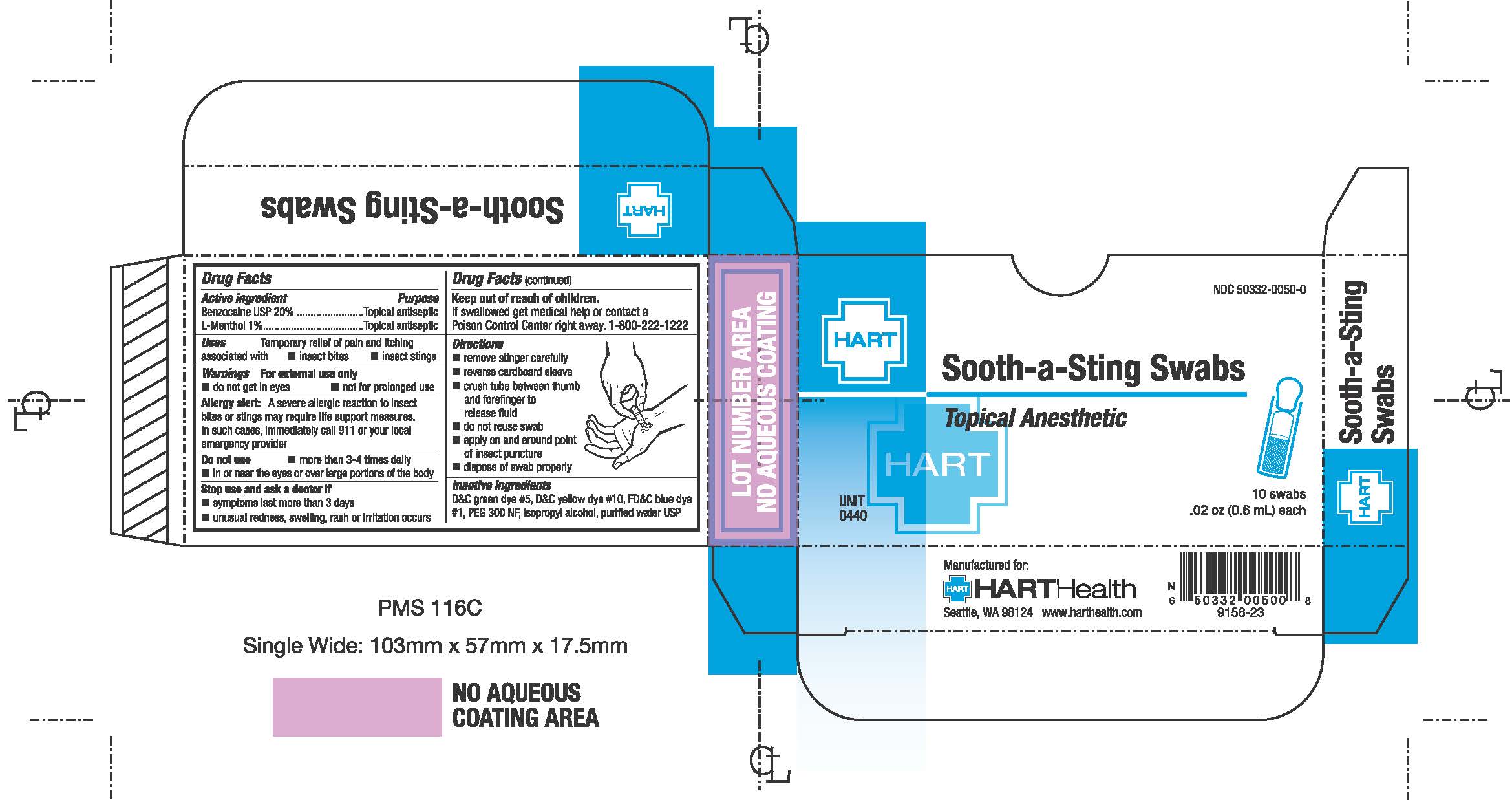 DRUG LABEL: Sooth-a-Sting
NDC: 50332-0050 | Form: SWAB
Manufacturer: HART Health
Category: otc | Type: HUMAN OTC DRUG LABEL
Date: 20240118

ACTIVE INGREDIENTS: BENZOCAINE 0.12 g/0.6 mL; MENTHOL, UNSPECIFIED FORM .006 g/0.6 mL
INACTIVE INGREDIENTS: ISOPROPYL ALCOHOL; WATER; D&C GREEN NO. 5; D&C YELLOW NO. 10; FD&C BLUE NO. 1; POLYETHYLENE GLYCOL 300

SOOTH-A-STING SWABS

Active Ingredients

Benzocaine 20%

L-Menthol 1%

Purpose

Topical Anesthetic

Topical Anesthetic

Uses

Temporarily relief of pain and itching associated with

- insect bites
- insect stings

Warnings

For external use only

- do not get in eyes
- not for prolonged use

Allergy alert: A severe allertig reaction to insect bites and stings may require life support measures. In such cases, immediately call 911 or your local emergency provider.

Do not use

- in or near the eyes or over large portions of the body
- more than 3-4 times daily

Stop use and ask a doctor if

- condition persists
- unusual redness, swelling, rash, or irritation occurs

Keep out of reach of children

If swallowed, get medical help or contact a Poison Control Center right away 1-800-222-1222

Directions

- remove stinger carefully
- reverse cardboard sleeve
- crush tube between thumb and forefinger to release fluid
- apply on and aroundpoint of insect puncture
- do not reuse swab
- dispose of swab properly

Inactive Ingredient

D&C green dye#5, D&C yellow dye #10, FD&C blue dye #1, PEG 300 NF, isopropyl alcohol, purified water USP